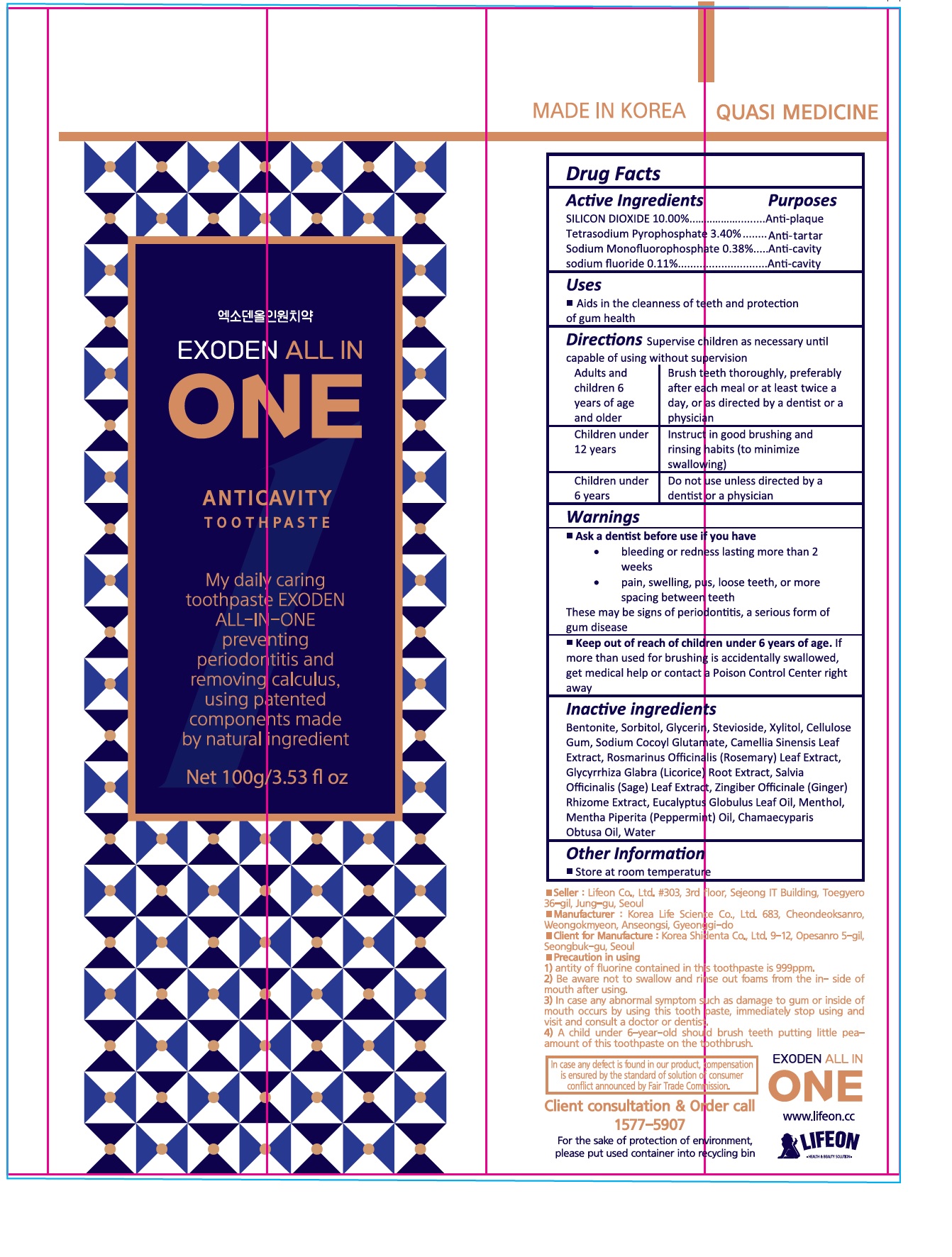 DRUG LABEL: EXODEN ALL IN ONE
NDC: 70602-010 | Form: PASTE
Manufacturer: LIFEON Corp.
Category: otc | Type: HUMAN OTC DRUG LABEL
Date: 20220713

ACTIVE INGREDIENTS: SODIUM PYROPHOSPHATE 3.4 g/100 g; SILICON DIOXIDE 10 g/100 g; SODIUM MONOFLUOROPHOSPHATE 0.38 g/100 g; SODIUM FLUORIDE 0.11 g/100 g
INACTIVE INGREDIENTS: BENTONITE; SORBITOL; GLYCERIN; STEVIOSIDE; XYLITOL; CARBOXYMETHYLCELLULOSE SODIUM, UNSPECIFIED; SODIUM COCOYL GLUTAMATE; GREEN TEA LEAF; ROSEMARY; GLYCYRRHIZA GLABRA; SAGE; GINGER; EUCALYPTUS OIL; MENTHOL, UNSPECIFIED FORM; PEPPERMINT OIL; CHAMAECYPARIS OBTUSA WOOD OIL; WATER

70602-010_EXODEN ALL IN ONE TOOTHPASTE

ACTIVE INGREDIENT

Silicon dioxide 10%

Tetrasodium Pyrophosphate 3.40%

Sodium Monofluorophosphate 0.38%

sodium fluoride 0.11%

PURPOSE

Anti plaque

Anti tartar

Anti cavity

INDICATIONS AND USAGE

Aids in cleanness of teeth and protection of gum health

DOSAGE AND ADMINISTRATION

Supervise children as necessary until capable of using without supervision

Adults and children 6 years of age and older: Brush teeth thoroughly, preferably after each meal or at least twice a day, or as directed by a dentist or a physician

Children under 12 years: Instruct in good brushing and rinsing habits (to minimize swallowing)

Children under 6 years: Do not use unless directed by a dentist or a physician

WARNINGS

Ask a dentist before use if you have
• bleeding or redness lasting more than 2 weeks
• pain, swelling, pus, loose teeth, or more spacing between teeth
These may be signs of periodontitis, a serious form of gum disease

Keep out of reach of children under 6 years of age. If more than used for brushing is accidentally swallowed, get medical help or contact a Poison Control Center right away

INACTIVE INGREDIENT

Bentonite, Sorbitol, Glycerin, Stevioside, Xylitol, Cellulose Gum, Sodium Cocoyl Glutamate, Camellia Sinensis Leaf Extract, Rosmarinus Officinalis (Rosemary) Leaf Extract, Glycyrrhiza Glabra (Licorice) Root Extract, Salvia Officinalis (Sage) Leaf Extract, Zingiber Officinale (Ginger) Rhizome Extract, Eucalyptus Globulus Leaf Oil, Menthol, Mentha Piperita (Peppermint) Oil, Chamaecyparis Obtusa Oil, Water